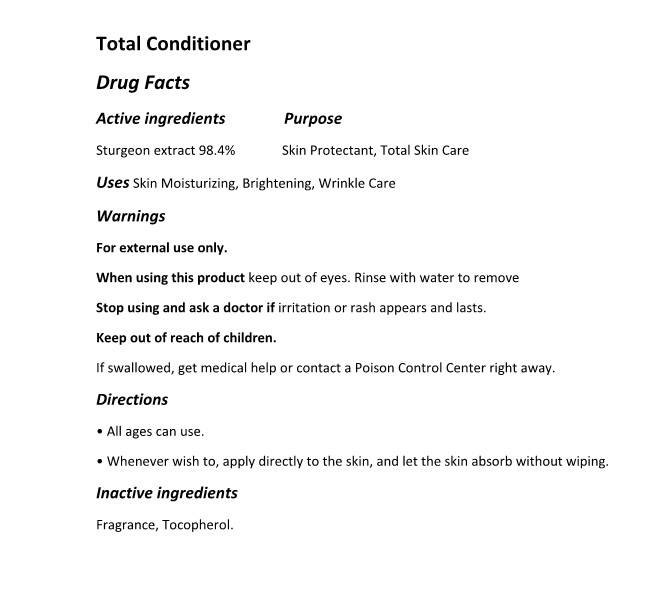 DRUG LABEL: The Zoeun Skin Total Conditioner
NDC: 83636-602 | Form: SPRAY
Manufacturer: Sturgeonbio Co.,Ltd
Category: otc | Type: HUMAN OTC DRUG LABEL
Date: 20250120

ACTIVE INGREDIENTS: STURGEON, UNSPECIFIED 98.4 g/100 mL
INACTIVE INGREDIENTS: TOCOPHEROL; FRAGRANCE 13576

83636-602 The Zoeun Skin Total Conditioner

Active Ingredients

Sturgeon extract 98.4%

Purposes

Skin Protectant, Total Skin Care

Uses

Skin Moisturizing, Brightening, Wrinkle Care

Warnings

Keep out of reach of children.
If swallowed, get medical help or contact a Poison Control Center right away.

Warnings

Stop using and ask a doctor if irritation or rash appears and lasts.

Warnings

When using this product keep out of eyes. Rinse with water to remove.

Warnings

For external use only.

Directions

• All ages can use.
• Whenever wish to, apply directly to the skin, and let the skin absorb without wiping.

Inactive Ingredients

Fragrance, Tocopherol.